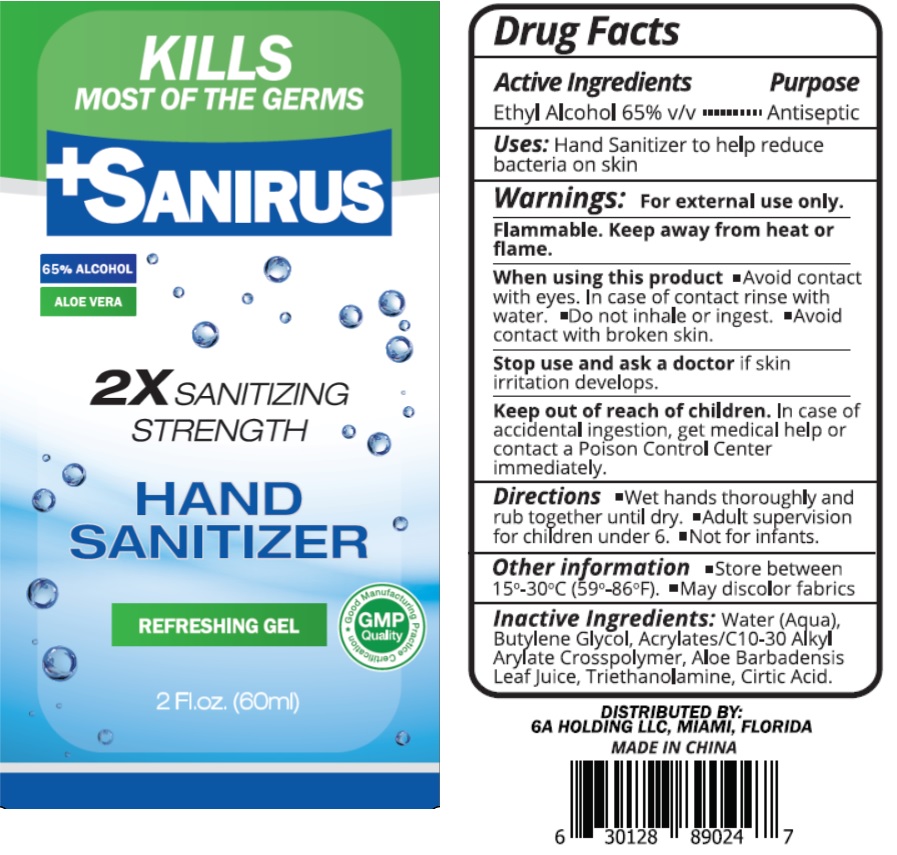 DRUG LABEL: SANIRUS HAND SANITIZER
NDC: 74691-002 | Form: GEL
Manufacturer: 6A Holding, LLC
Category: otc | Type: HUMAN OTC DRUG LABEL
Date: 20200608

ACTIVE INGREDIENTS: ALCOHOL 65 mL/100 mL
INACTIVE INGREDIENTS: WATER; BUTYLENE GLYCOL; CARBOMER INTERPOLYMER TYPE A (ALLYL SUCROSE CROSSLINKED); ALOE VERA LEAF; TROLAMINE; CITRIC ACID MONOHYDRATE

Sanirus Hand Sanitizer 65

Active Ingredients

Ethyl Alcohol 65% v/v

Purpose

Antiseptic

INDICATIONS AND USAGE

Uses: Hand Sanitizer to help reduce bacteria on skin

Warnings: For external use only.

Flammable. keep away from heat or flame.

When using this product • Avoid contact with eyes. In case of contact rinse with water. • Do not inhale or ingest. • Avoid contact with broken skin.

Stop use and ask a doctor if skin irritation develops.

Keep out of reach of children. In case of accidental ingestion, get medical help or contact a Poison Control Center immediately

DOSAGE AND ADMINISTRATION

Directions • Wet hands thoroughly and rub together until dry. • Adult supervision for children under 6. • Not for infants.

Other information • Store between 15°-30°C (59°-86°F). • May discolor fabrics

INACTIVE INGREDIENT

Inactive Ingredients: Water (Aqua), Butylene Glycol, Acrylates/C10-30 Alkyl Acrylate Crosspolymer, Aloe Barbadensis Leaf Juice, Triethanolamine, Citric Acid.

KILLS MOST OF THE GERMS

65% ALCOHOL

ALOE VERA

2X SANITIZING STRENGTH

REFRESHING GEL

GMP Quality

DISTRIBUTED BY: 6A HOLDING LLC, MIAMI, FLORIDA

MADE IN CHINA